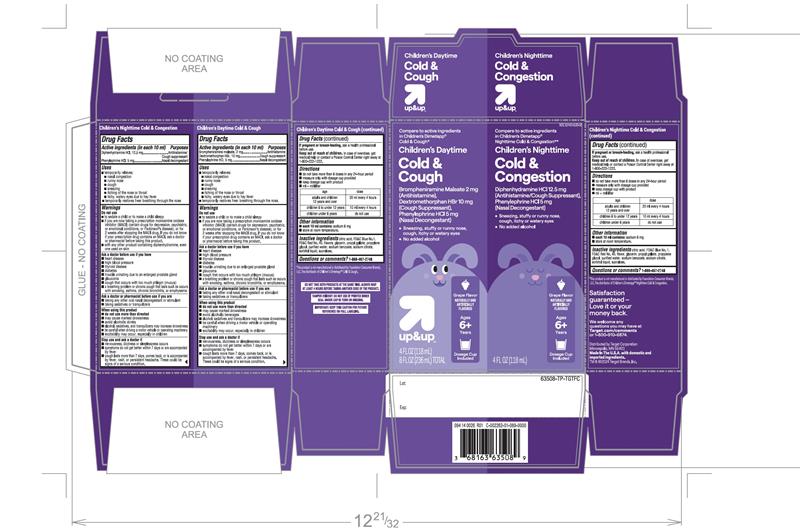 DRUG LABEL: TARGET CHILDRENS DT AND NT COLD and COUGH
NDC: 82442-536 | Form: KIT | Route: ORAL
Manufacturer: TARGET CORPORATION
Category: otc | Type: HUMAN OTC DRUG LABEL
Date: 20251105

ACTIVE INGREDIENTS: BROMPHENIRAMINE MALEATE 2 mg/10 mL; DEXTROMETHORPHAN HYDROBROMIDE 10 mg/10 mL; PHENYLEPHRINE HYDROCHLORIDE 5 mg/10 mL; DIPHENHYDRAMINE HYDROCHLORIDE 12.5 mg/10 mL; PHENYLEPHRINE HYDROCHLORIDE 5 mg/10 mL
INACTIVE INGREDIENTS: ANHYDROUS CITRIC ACID; FD&C BLUE NO. 1; FD&C RED NO. 40; GLYCERIN; PROPYL GALLATE; PROPYLENE GLYCOL; WATER; SODIUM BENZOATE; SODIUM CITRATE, UNSPECIFIED FORM; SORBITOL; SUCRALOSE; ANHYDROUS CITRIC ACID; FD&C BLUE NO. 1; FD&C RED NO. 40; GLYCERIN; PROPYL GALLATE; PROPYLENE GLYCOL; WATER; SODIUM BENZOATE; SODIUM CITRATE, UNSPECIFIED FORM; SORBITOL; SUCRALOSE

TARGET Children’s Daytime & Nighttime Value Pack Drug Facts

Children’s Daytime Cold & Cough Active ingredients (in each 10 mL)

Brompheniramine maleate, 2 mg

Dextromethorphan HBr, 10 mg

Phenylephrine HCl, 5 mg

Children’s NighttimeCold & Congestion Active ingredients (in each 10 mL)

Diphenhydramine HCL12.5 mg

Phenylephrine HCL5 mg

Purposes forChildren’s Daytime Cold & Cough

Antihistamine

Cough suppressant

Nasal decongestant

Purposes forChildren’s NighttimeCold & Congestion

Antihistamine/Cough suppressant

Nasal decongestant

Uses

Daytime

- temporarily relieves
  - nasal congestion
  - runny nose
  - cough
  - sneezing
  - itching of the nose or throat
  - itchy, watery eyes due to hay fever
  - temporarily restores freer breathing through the nose.

Nighttime

- temporarily relieves
  - nasal congestion
  - runny nose
  - cough
  - sneezing
  - itching of the nose or throat
  - itchy, watery eyes due to hay fever
  - temporarily restores freer breathing through the nose.

Warnings Do not use

Daytime

- to sedate a child or to make a child sleepy
- if you are now taking a prescription monoamine oxidase inhibitor (MAOI) (certain drugs for depression, psychiatric, or emotional conditions, or Parkinson's disease), or for 2 weeks after stopping the MAOI drug. If you do not know if your child's prescription drug contains an MAOI, ask a doctor or pharmacist before giving this product.

Nighttime only

- to sedate a child or to make a child sleepy
- if you are now taking a prescription monoamine oxidase inhibitor (MAOI) (certain drugs for depression, psychiatric, or emotional conditions, or Parkinson's disease), or for 2 weeks after stopping the MAOI drug. If you do not know if your child's prescription drug contains an MAOI, ask a doctor or pharmacist before giving this product.
- With any other product containing diphenhydramine, even one used on skin

Ask a doctor before use if you have

DAYTIME

- heart disease
- high blood pressure
- diabetes
- thyroid disease
- trouble urinating due to an enlarged prostate gland
- glaucoma
- cough that occurs with too much phlegm (mucus)
- a breathing problem or chronic cough that lasts such as occurs with smoking, asthma, chronic bronchitis, or emphysema.

NIGHTTIME

- heart disease
- high blood pressure
- diabetes
- thyroid disease
- trouble urinating due to an enlarged prostate gland
- glaucoma
- cough that occurs with too much phlegm (mucus)
- a breathing problem or chronic cough that lasts such as occurs with smoking, asthma, chronic bronchitis, or emphysema.

Ask a doctor or pharmacist before use if you are

DAYTIME

- taking any other oral nasal decongestant or stimulant
- taking sedatives or tranquilizers

NIGHTTIME

- taking any other oral nasal decongestant or stimulant
- taking sedatives or tranquilizers

When using this product

Daytime

- do not use more than directed.
- may cause marked drowsiness
- avoid alcohol, sedatives and tranquilizers may increase drowsiness
- be careful when driving a motor vehicle or operating machinery
- excitability may occur, especially in children

Nighttime

- do not use more than directed.
- may cause marked drowsiness
- avoid alcohol, sedatives and tranquilizers may increase drowsiness
- be careful when driving a motor vehicle or operating machinery
- excitability may occur, especially in children

Stop use and ask a doctor if

DAYTIME

- nervousness, dizziness, or sleeplessness occur
- symptoms do not get better with 7 days or are accompanied with fever
- cough lasts more than 7 days, comes back, or is accompanied by fever, rash, or headache.

These could be signs of a serious condition.

NIGHTTIME

- nervousness, dizziness, or sleeplessness occur
- symptoms do not get better with 7 days or are accompanied with fever
- cough lasts more than 7 days, comes back, or is accompanied by fever, rash, or headache.

These could be signs of a serious condition.

Keep out of reach of children.

Daytime

In case of overdose, get medical help or contact a Poison Control Center right away at 1-800-222-1222.

Nighttime

In case of overdose, get medical help or contact a Poison Control Center right away at 1-800-222-1222.

If pregnant or breast-feeding,

Ask a health professional before use

Directions

Daytime

- do not take more than 6 doses in any 24-hour period
- measure only with dosing cup provided.
- Keep dosage cup with product
- mL= milliliter

age | dose
Adults and children 12 years and over | 20 mL every 4 hours
children 6 to under 12 years | 10 mL every 4 hours
children under 6 years of age | do not use

Nighttime

- do not take more than 6 doses in any 24-hour period
- measure only with dosing cup provided.
- Keep dosage cup with product
- mL= milliliter

age | dose
Adults and children 12 years and over | 20 mL every 4 hours
children 6 to under 12 years | 10 mL every 4 hours
children under 6 years of age | do not use

Other information

Daytime

- each 10 mL contains:sodium 6 mg
- store at room temperature.

Nighttime

- each 10 mL contains:sodium 6 mg
- store at room temperature.

Inactive ingredients

Inactive ingredients for Day Time

anhydrous citric acid, FD&C blue #1, FD&C red #40, flavor, glycerin, propyl gallate, propylene glycol, purified water, sodium benzoate, sodium citrate, sorbitol, sucralose

Inactive ingredients for Nighttime

anhydrous citric acid, FD&C blue #1, FD&C red #40, flavor, glycerin, propyl gallate, propylene glycol, purified water, sodium benzoate, sodium citrate, sorbitol, sucralose

Questions or comments?

1-866-467-2748

Principal Display Panel

Compare to the active ingredients in Children's Dimetapp® Cold & Cough*

Children's Daytime

Cold & Cough

Brompheniramine Maleate 2 mg (Antihistamine),

Dextromethorphan HBr 10 mg (Cough Suppressant)

Phenylephrine HCI 5 mg (Nasal Decongestant)

- Sneezing, stuffy or runny nose, cough, itchy or watery eyes
- No added alcohol

Dosing Cup Included

Ages 6+ Years

Grape Flavor

NATURALLY AND ARTIFICIALLY FLAVORED

4 FL OZ (118mL)

Compare to the active ingredients in Children's Dimetapp® Nighttime Cold & Congestion**

Children's Nighttime

Cold & Congestion

Diphenhydramine HCI 12.5 mg (Antihistamine / Cough Suppressant)

Phenylephrine HCI 5 mg (Nasal Decongestant)

- Sneezing, stuffy or runny nose, cough, itchy or watery eyes
- No added alcohol

Dosing Cup Included

Ages 6+ Years

Grape Flavor

NATURALLY AND ARTIFICIALLY FLAVORED

4 FL OZ (118mL)

8 FL OZ (236 mL) TOTAL

DO NOT TAKE BOTH PRODUCTS AT THE SAME TIME. ALWAYS WAIT AT LEAST 4 HOURS BEFORE TAKING ANOTHER DOSE OF THE PRODUCT.

TAMPER EVIDENT: DO NOT USE IF PRINTED SAFETY SEAL AROUND BOTTLE OR UNDER CAP IS BROKEN OR MISSING

IMPORTANT:KEEP THIS CARTON FOR FUTURE REFERENCE FOR FULL LABELING

*This product is not manufactured or distributed by Foundation Consumer Brands, LLC, the distributor of Children's Dimetapp® Cold & Congestion.

Satisfaction guaranteed – Love it or your money back

We welcome any questions you may have at

Target.com/comments

Or 1-800-910-6874.

Distributed by: Target Corporation

Minneapolis, MN 55403

Made in the U.S.A. with domestic and imported ingredients

TM & ©2024 Target Brands, Inc,